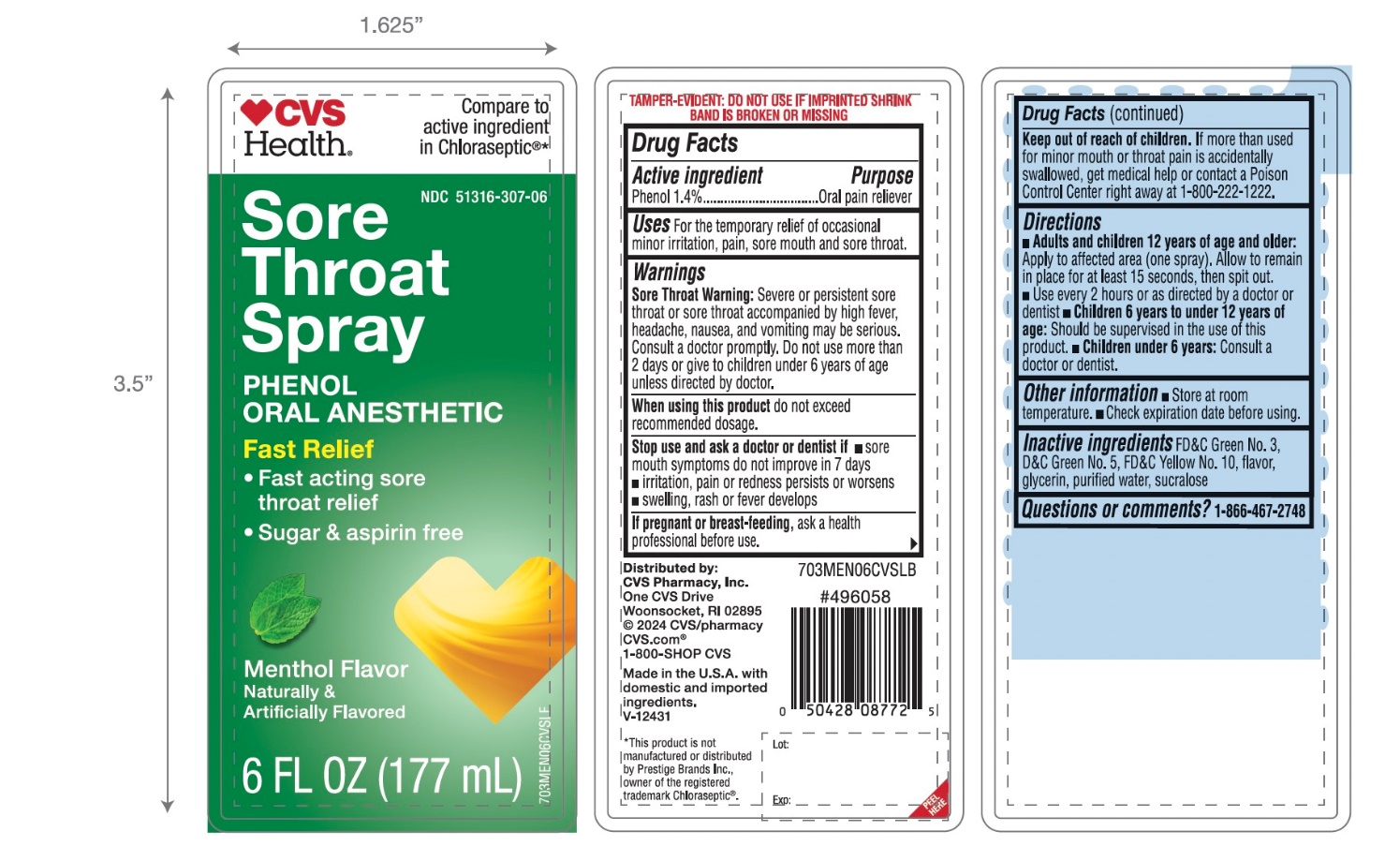 DRUG LABEL: CVS Sore Throat

NDC: 51316-307 | Form: SPRAY
Manufacturer: CVS PHARMACY,INC.
Category: otc | Type: HUMAN OTC DRUG LABEL
Date: 20251209

ACTIVE INGREDIENTS: PHENOL 1.4 g/100 mL
INACTIVE INGREDIENTS: FD&C GREEN NO. 3; D&C GREEN NO. 5; D&C YELLOW NO. 10; GLYCERIN; WATER; SUCRALOSE

CVS Sore Throat Spray

Active ingredient

Phenol 1.4%

Purpose

Oral pain reliever

Uses

For the temporarily relief of occasional minor irritation, pain, sore mouth and sore throat.

Warnings

Sore throat warning:Severe or persistent sore throat or sore throat accompanied by high fever, headache, nausea, and vomiting may be serious. Consult a doctor promptly. Do not use more than 2 days or give to children under 6 year of age unless directed by doctor.

When using this product,

do not exceed recommended dosage.

Stop use and ask a doctor or dentist if

- sore mouth symptoms do not improve in 7 days
- irritation, pain or redness persists or worsens
- swelling, rash or fever develops

If pregnant or breast-feeding,

ask a health professional before use.

Keep out of reach of children.

If more than used for minor mouth or throat pain is accidently swallowed,get medical help or contact a Poison Control Center right away 1-800-222-1222.

Directions

- Adults and children 12 year of age and older:

Apply to affected area (one spray). Allow to remain in place for at least 15 seconds, then spit out.

Use every 2 hours or as directed by a doctor or dentist

- Children 6 years to under 12 years of age:Should be supervised in use of this product.
- Children under 6 years of age: Ask a doctor or dentist

Other information

- store at room temperature
- Check expiration date before using.

Inactive ingredients

FD&C Green No.3, D&C Green No. 5, D&C Yellow No.10, flavor, glycerin, purified water, sucralose.

Questions or comments?

1-866-467-2748

Principal Display Panel

*Compare to the active ingredient in Chloraseptic®

NDC 51316-307-06

SORE THROAT SPRAY

Phenol / Oral Pain Reliever

- Fast Acting
- Numbs on Contact

SUGAR FREE

ASPIRIN FREE

MENTHOL FLAVOR

Naturally and Artificially Flavored

6 FL OZ (177 mL)

*This product is not manufactured or distributed by Prestige Brands Inc., owner of the registered trademark Chloraseptic®.

Tamper Evident: Do not use if imprinted shrink band is broken or missing.

Distributed by: